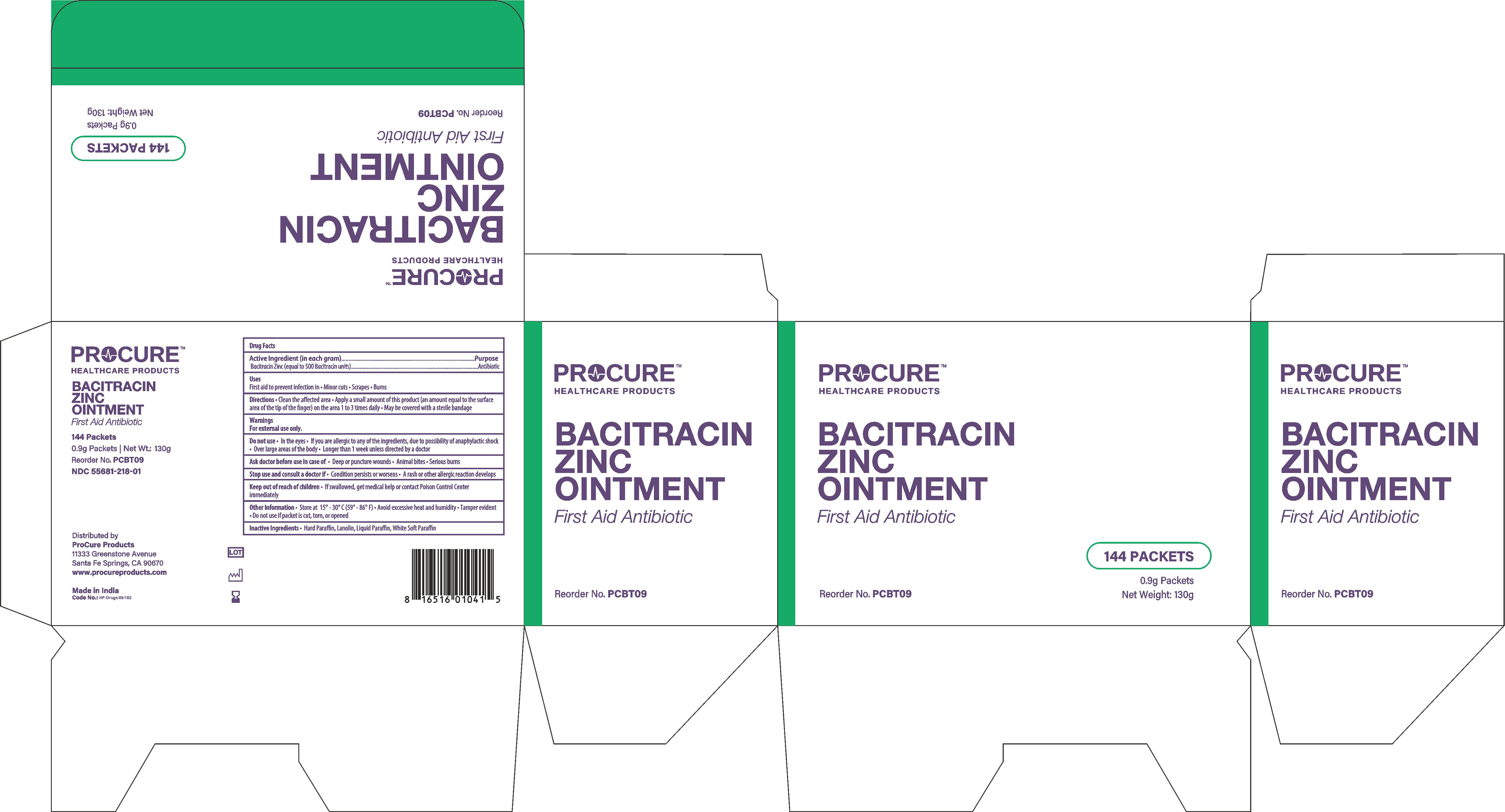 DRUG LABEL: procureFirst Aid Antibio
NDC: 55681-218 | Form: OINTMENT
Manufacturer: TWIN MED, LLC
Category: otc | Type: HUMAN OTC DRUG LABEL
Date: 20250620

ACTIVE INGREDIENTS: BACITRACIN ZINC 500 U/1 g
INACTIVE INGREDIENTS: PARAFFIN; LANOLIN; MINERAL OIL; PETROLATUM

Drug Facts

Active Ingredients(in each gram)

Bacitracin Zinc (equal to 500 Bacitracin units)

Purpose

Antibiotic

Uses

First aid to prevent infection in Minor cuts, Scrapes & Burns

Directions

- Clean the affected area
- Apply small amount of this product(an amount equal to the surface area of the tip of the finger) on the area 1 to 3 times daily
- May be covered with a sterile bandage

Warnings

For External Use Only.

Do not use

- In the eyes
- If you are allergic to any of the ingredients, due to possibility of anaphylactic shock
- Over large areas of the body
- Longer than 1 week unless directed by a doctor
- Ask a doctor before use in case of deep or puncture wounds, animal bites or serious burns

Stop use and ask a doctor if

- The condition persists or gets worse
- A rash or allergic reaction develops

Keep out of reach of children

- If swallowed, get medical help or contact a Poison Control Centre right away

Other information

- Store at controlled room temperature 15o- 30oC(59o--86oF)
- Avoid excessive heat and humidity
- Tamper Evident
- Do not use if packet is torn, cut, or opened.

Inactive Ingredients

Hard Paraffin, Lanolin, Liquid Paraffin,White Soft Paraffin